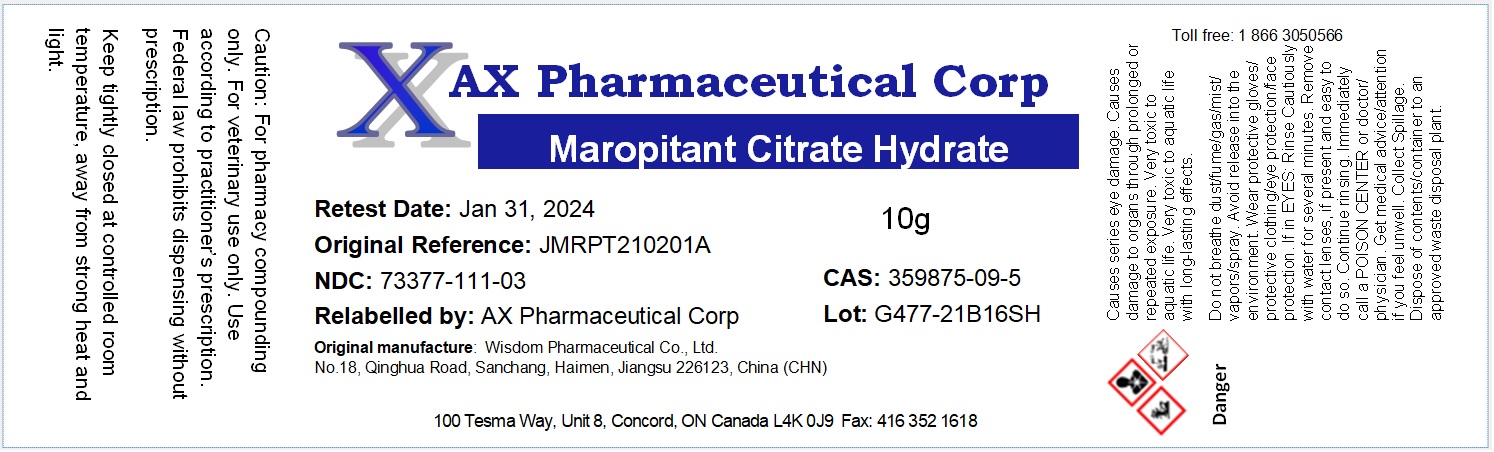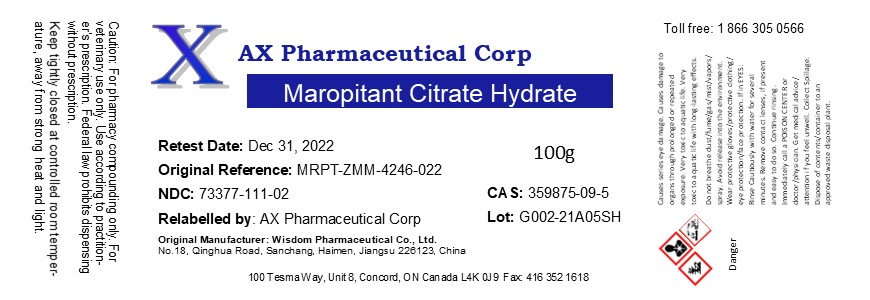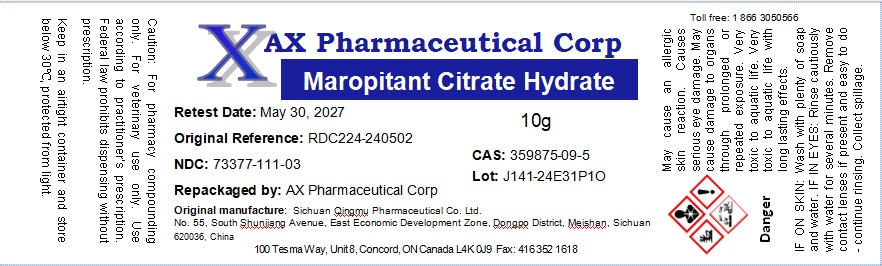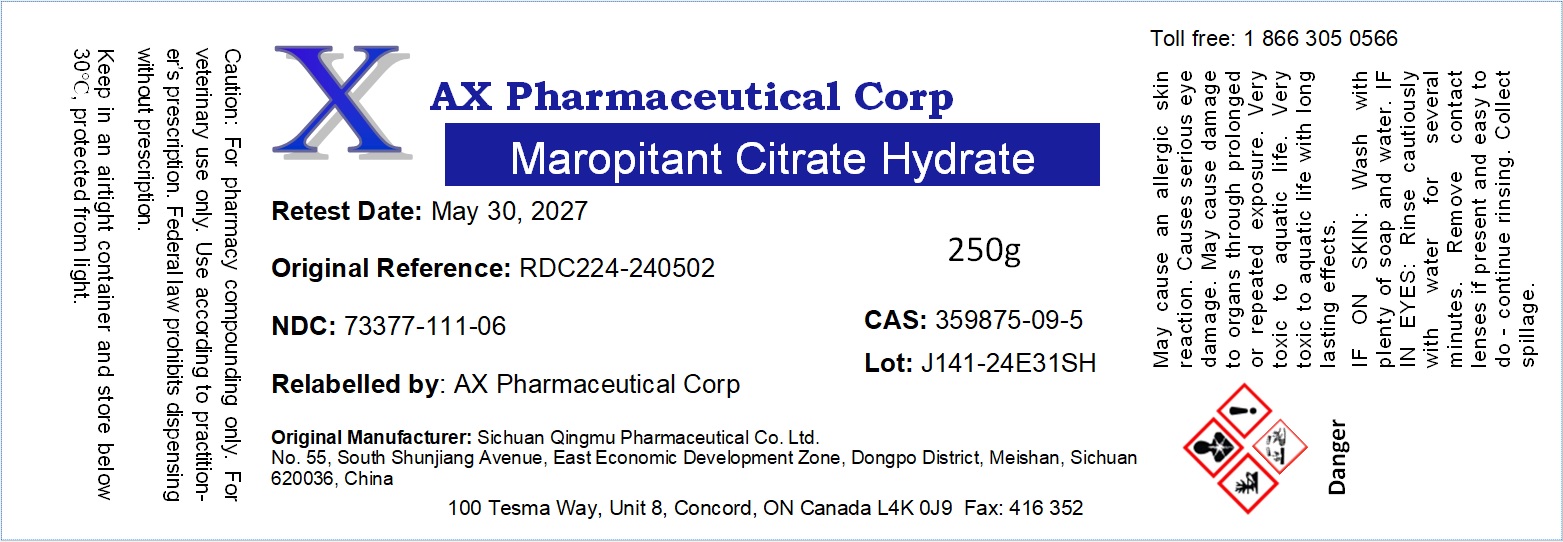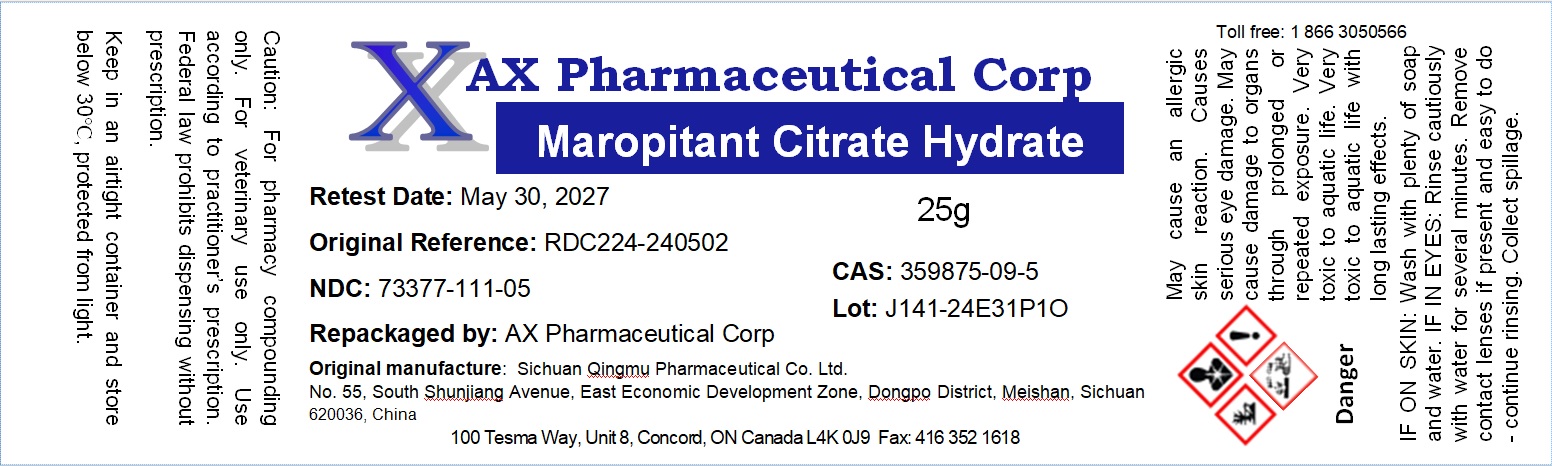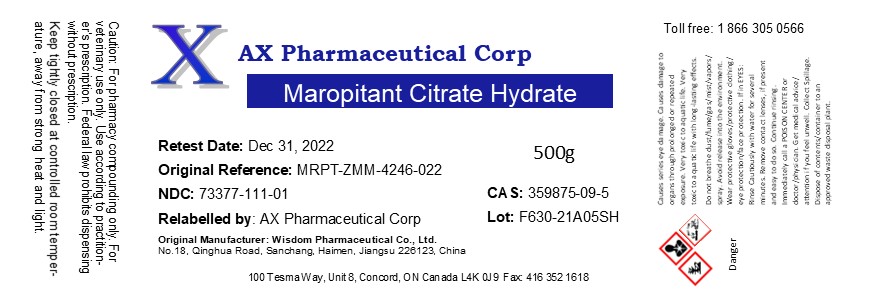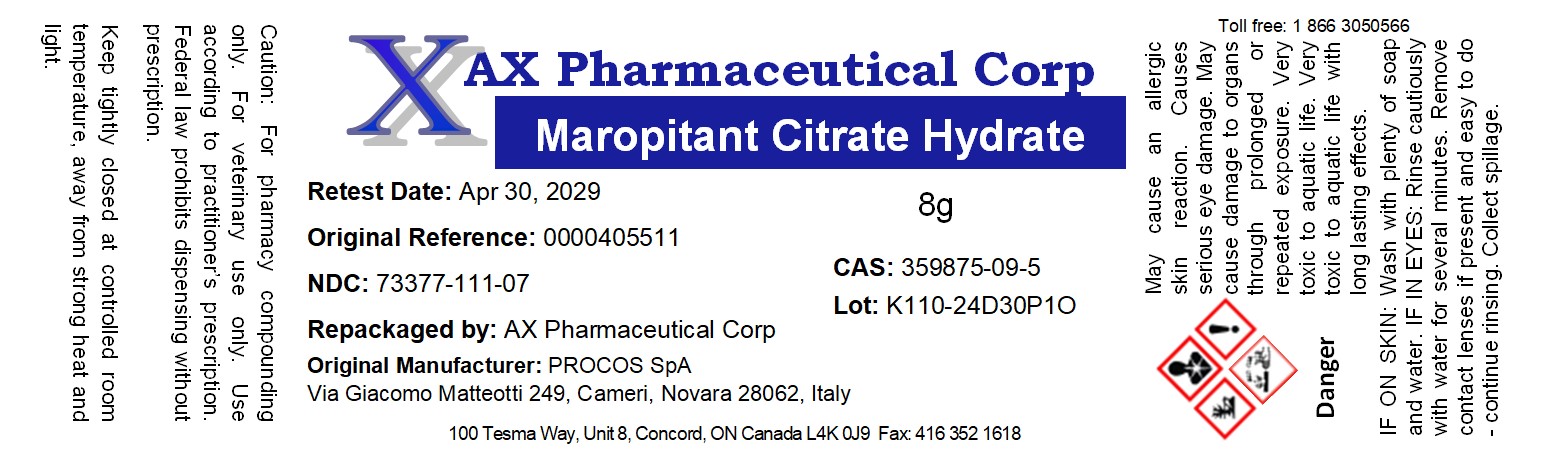 DRUG LABEL: Maropitant Citrate Hydrate
NDC: 73377-111 | Form: POWDER
Manufacturer: AX Pharmaceutical Corp
Category: other | Type: BULK INGREDIENT - ANIMAL DRUG
Date: 20250805

ACTIVE INGREDIENTS: MAROPITANT CITRATE 1 g/1 g

Maropitant Citrate Hydrate